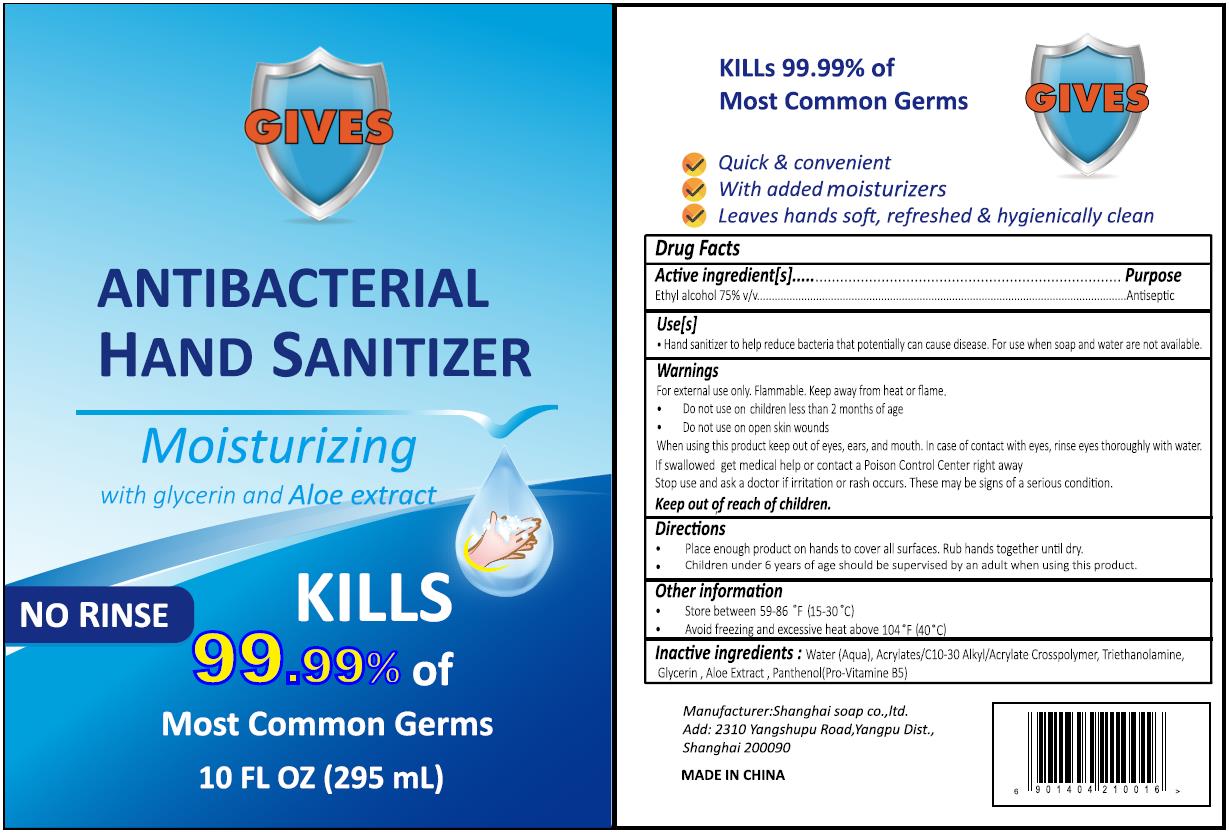 DRUG LABEL: HAND SANITIZER
NDC: 76390-0105 | Form: GEL
Manufacturer: Shanghai Soap Co., Ltd.
Category: otc | Type: HUMAN OTC DRUG LABEL
Date: 20200611

ACTIVE INGREDIENTS: ALCOHOL 221.25 mL/295 mL
INACTIVE INGREDIENTS: GLYCERIN; WATER; CARBOMER INTERPOLYMER TYPE A (ALLYL SUCROSE CROSSLINKED); TROLAMINE; DEXPANTHENOL; ALOE

SSC, Sanitizer, 75% Alcohol, Gel; 295mL

Active Ingredient(s)

Ethyl alcohol 75% v/v. Purpose: Antiseptic

Purpose

Antiseptic

Use

Hand sanitizer to help reduce bacteria that potentially can cause disease.

For use when soap and water are not available.

Warnings

For external use only. Flammable. Keep away from heat or flame.

- Do not use on children less than 2 months of age
- Do not use on open skin wounds

When using this product keep out of eyes, ears, and mouth.

If case of contact with eyes, rinse eyes thoroughly with water.

Stop use and ask a doctor if irritation or rash occurs.

Thess may be signs of a serious condition.

Keep out of reach of children.

Directions

- Place enough product on hands to cover all surfaces. Rub hands together until dry.
- Children under 6 years of age should be supervised by an adult when using this product.

Other information

Store between 59-86 ℉ (15-30 ℃).

Avoid freezing and excessive heat above 104 ℉ (40 ℃).

Inactive ingredients

Water (Aqua), Acrylates/C10-30 Alkyl/Acrylate Crosspolymer, Triethanolamine, Glycerin, Aloe Extract, Panthenol (pro-Vitamin B5)